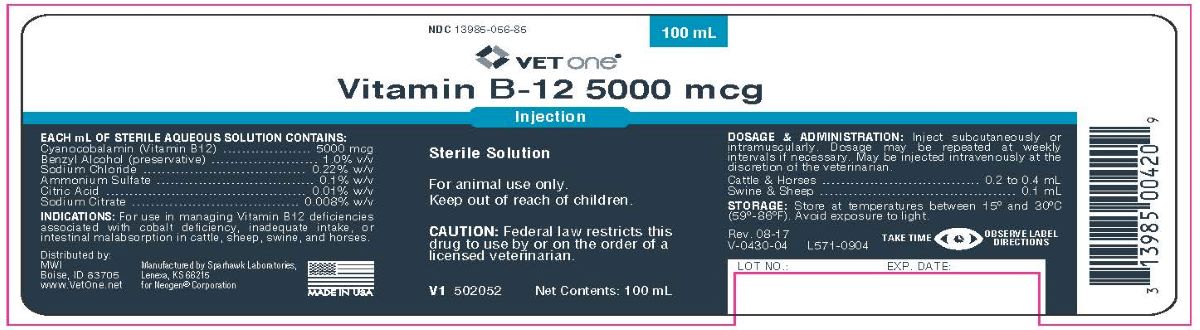 DRUG LABEL: Vitamin B-12 5000 mcg
NDC: 13985-056 | Form: INJECTION
Manufacturer: MWI/Vet One
Category: animal | Type: PRESCRIPTION ANIMAL DRUG LABEL
Date: 20240102

ACTIVE INGREDIENTS: CYANOCOBALAMIN 5 mg/1 mL
INACTIVE INGREDIENTS: BENZYL ALCOHOL; WATER; SODIUM CHLORIDE; AMMONIUM SULFATE; ANHYDROUS CITRIC ACID; SODIUM CITRATE

Vitamin B-12 5000 mcg
Injection

INDICATIONS:

For use in managing Vitamin B12 deficiencies associated with cobalt deficiency, inadequate intake, or intestinal malabsorption in
cattle, sheep, swine, and horses.

EACH mL OF STERILE AQUEOUS SOLUTION CONTAINS:

Cyanocobalamin (Vitamin B12)..............5000 mcg

Benzyl Alcohol (preservative).................1.0% v/v

Sodium Chloride.................................0.22% w/v

Ammonium Sulfate...............................0.1% w/v

Citric Acid..........................................0.01% w/v

Sodium Citrate..................................0.008% w/v

DOSAGE & ADMINISTRATION:

Inject subcutaneously or intramuscularly. Dosage may be repeated at weekly intervals if necessary. May be injected intravenously at the discretion of the veterinarian.

Cattle and Horses ............................... 0.2 to 0.4 mL

Swine and Sheep .......................................... 0.1 mL

STORAGE:

Store at temperature between 15° and 30°C (59° - 86°F). Avoid exposure to light.

Rev. 08-17

V-0430-04 L571-0904

TAKE TIME OBSERVE LABEL DIRECTIONS

Distributed by:
MWIBoise, ID 83705
www.VetOne.net
Manufactured by Sparhawk Laboratories,
Lenexa, KS 66215
for Neogen® Corporation
MADE IN USA